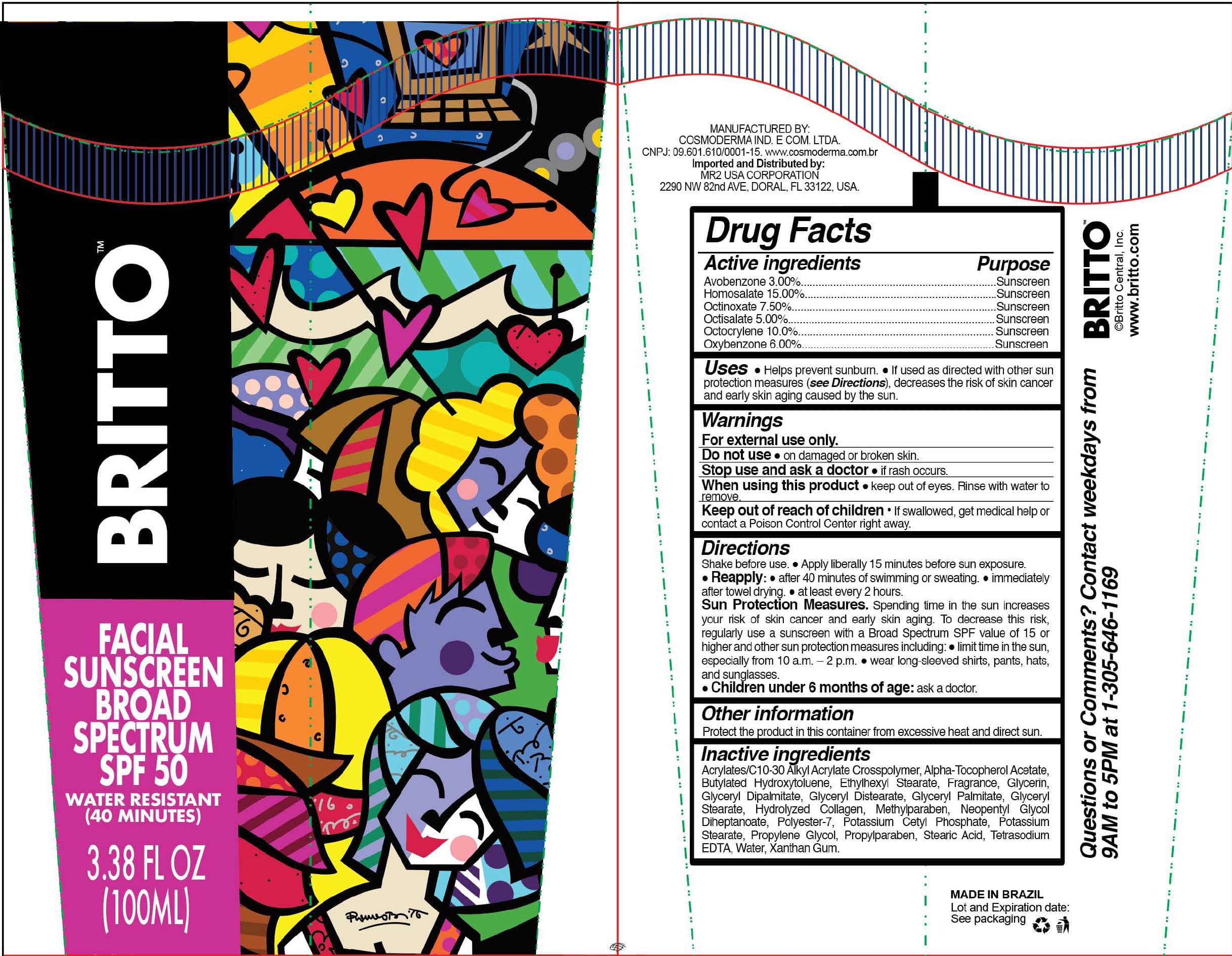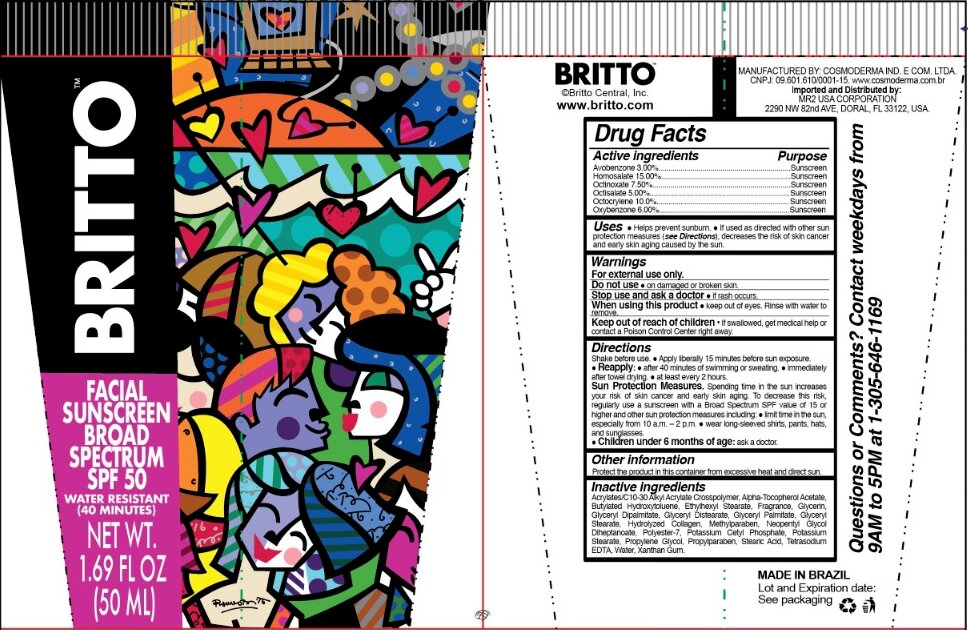 DRUG LABEL: Britto Facial Sunscreen Broad Spectrum SPF 50
NDC: 77069-003 | Form: CREAM
Manufacturer: MR2 USA Corporation
Category: otc | Type: HUMAN OTC DRUG LABEL
Date: 20201227

ACTIVE INGREDIENTS: OCTINOXATE 7.5 g/100 mL; OXYBENZONE 6 g/100 mL; HOMOSALATE 15 g/100 mL; OCTOCRYLENE 10 g/100 mL; OCTISALATE 5 g/100 mL; AVOBENZONE 3 g/100 mL
INACTIVE INGREDIENTS: GLYCERYL MONOSTEARATE 2.24 g/100 mL; POTASSIUM CETYL PHOSPHATE 1 g/100 mL; POLYESTER-7 0.6 g/100 mL; NEOPENTYL GLYCOL DIHEPTANOATE 0.4 g/100 mL; .ALPHA.-TOCOPHEROL ACETATE 1 g/100 mL; XANTHAN GUM 0.2 g/100 mL; EDETATE SODIUM 0.05 g/100 mL; WATER 34.55 g/100 mL; POTASSIUM STEARATE 0.36 g/100 mL; ETHYLHEXYL STEARATE 3 g/100 mL; METHYLPARABEN 0.2 g/100 mL; PROPYLPARABEN 0.1 g/100 mL; BUTYLATED HYDROXYTOLUENE 0.1 g/100 mL; GLYCERYL DISTEARATE 1.84 g/100 mL; GLYCERYL PALMITATE 1.32 g/100 mL; CARBOMER COPOLYMER TYPE B (ALLYL PENTAERYTHRITOL CROSSLINKED) 0.2 g/100 mL; STEARIC ACID 0.6 g/100 mL; PROPYLENE GLYCOL 2 g/100 mL; GLYCERYL DIPALMITATE 1.32 g/100 mL; GLYCERIN 0.32 g/100 mL; PORK COLLAGEN 2 g/100 mL

NO CHANGE NOTIFICATION

Principal Display Panel - Statement of identity

Britto Facial Sunscreen Broad Spectrum SPF 50 Water Resistant (40 minutes)

Drug Facts Panel - Active Ingredients

Avobenzone 3.00% ----- Sunscreen

Homosalate 15.00% ----- Sunscreen

Octinoxate 7.50% ----- Sunscreen

Octisalate 5.00% ----- Sunscreen

Octocrylene 10.00% ---- Sunscreen

Oxybenzone 6.00% ----- Sunscreen

Drug Facts Panel - Purpose

Purpose: sunscreen

Drug Facts Panel - Uses

- Helps prevent sunburn.
- If used as directed with other sun protection measures (see Directions), decreases the risk of skin cancer and early skin ageing caused by the sun

Drug Facts Panel - Warnings

For external use only.

Do not use on damaged or broken skin.

Stop use and ask a doctor if rash occurs.

When using this product keep out of eyes. Rinse with water to remove.

Keep out of reach of children. If swallowed, get medical help or contact a Poison Control Center right away.

Do not use on damaged or broken skin.

Stop use and ask a doctor if rash occurs.

Stop use and ask a doctor if rash occurs.

When using this product keep out of eyes. Rinse with water to remove.

Keep out of reach of children. If swallowed, get medical help or contact a Poison Control Center right away.

Drug Facts Panel - Directions

- Apply liberally 15 minutes before sun exposure.
- Reapply: - after 40 minutes of swimming or sweating. - immediately after towel drying. - at least every 2 hours.
- Sun Protection Measures. Spending time in the sun increases your risk of skin cancer and early skin aging. To decrease this risk, regularly use a sunscreen with a Broad Spectrum SPF value of 15 or higher and other sun protection measures including: · limit time in the sun, especially from 10 a.m.-2 p.m. · wear long-sleeved shirts, pants, hats, and sunglasses.
- Children under 6 months of age: ask a doctor.

Drug Facts Panel - Other information

Protect the product in this container from excessive heat and direct sun.

Drug Facts Panel - Inactive Ingredients

Acrylates/C10-30 Alkyl Acrylate Crosspolymer, Alpha-Tocopherol Acetate, Butylated Hydroxytoluene, Ethylhexyl Stearate, Fragrance, Glycerin, Glyceryl Dipalmitate, Glyceryl Distearate, Glyceryl Palmitate, Glyceryl Stearate, Hydrolyzed Collagen, Methylparaben, Neopentyl Glycol Diheptanoate, Polyester-7, Potassium Cetyl Phosphate, Potassium Stearate, Propylene Glycol, Propylparaben, Stearic Acid, Tetrasodium EDTA, Water, Xanthan Gum.

Questions or comments? Contact weekdays from 9AM to 5PM at 1-305-646-1169.

Package Label - Principal Display Panel

50 ml NDC 77069-003-01

100 ml NDC 77069-003-02